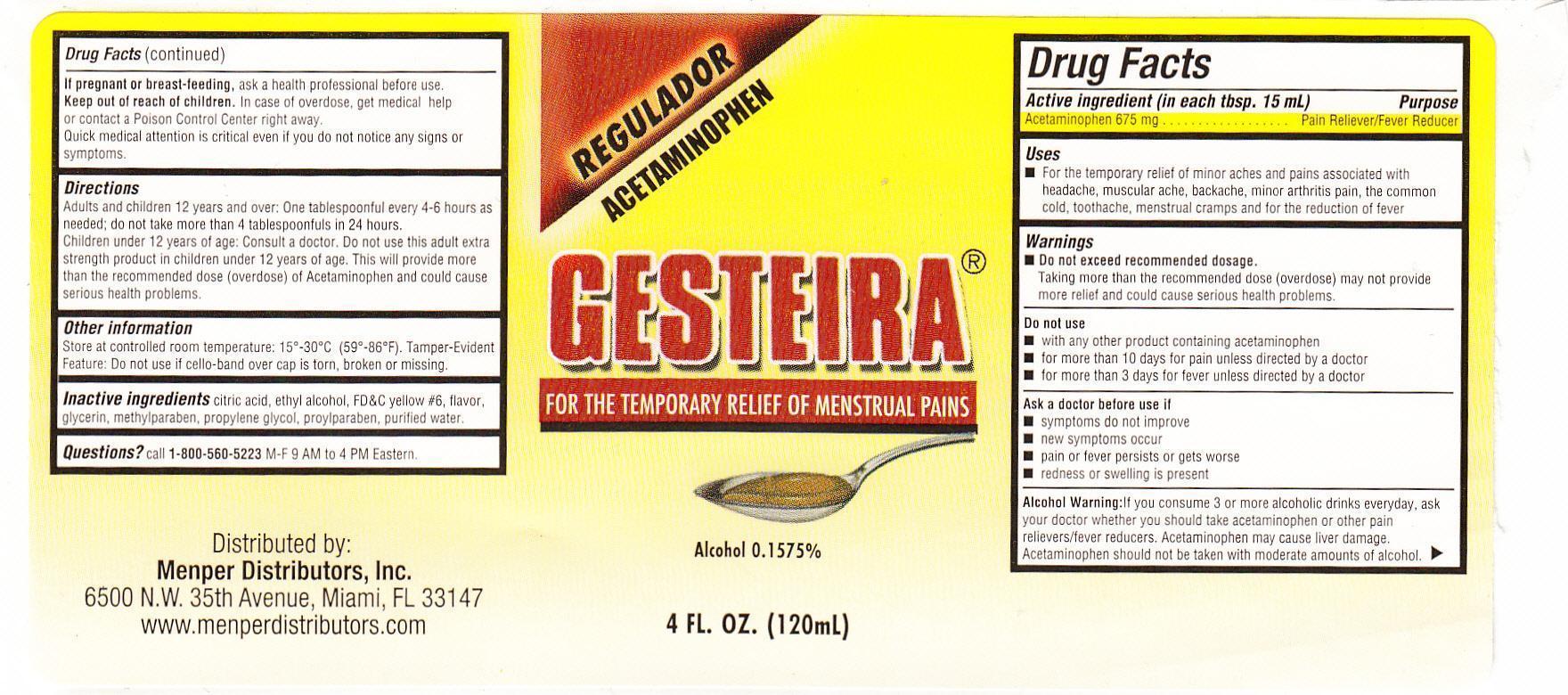 DRUG LABEL: Gesteira
NDC: 53145-052 | Form: LIQUID
Manufacturer: Menper Distributors, Inc.
Category: otc | Type: HUMAN OTC DRUG LABEL
Date: 20250722

ACTIVE INGREDIENTS: ACETAMINOPHEN 675 mg/15 mL
INACTIVE INGREDIENTS: D&C RED NO. 33; ANHYDROUS CITRIC ACID; ALCOHOL; FD&C RED NO. 40; GLYCERIN; METHYLPARABEN; PROPYLENE GLYCOL; PROPYLPARABEN; SODIUM CITRATE; SACCHARIN SODIUM; SUCRALOSE; SUCROSE; WATER

Gesteira

Active ingredient (in each tbsp. 15 mL)

Acetaminophen 675 mg

Purpose

Pain Reliever/ Fever Reducer

Uses

- For the temporary relief of minor aches and pains due to:
- the common cold
- headache
- backache
- minor pain of arthritis
- toothache
- muscular aches
- premenstrual and menstrual cramps
- temporarily reduces fever.

Warnings

Liver warning: This product contains acetaminophen. Sever liver damage may occur if you take

- more than 4,000 mg of acetaminophen in 24 hours
- with other drugs containing acetaminophen
- 3 or more alcoholic drinks every day while using this product

Allergy alert: acetaminophen may cause sever skin reaction. Symptoms may include:

- skin reddening
- blisters
- rash

If a skin reaction occurs, stop use and seek medical help right away.

Do not use

- with any other drug containing acetaminophen (prescription or nonprescription). If you are not sure whether a drug contains acetaminophen, ask a doctor or pharmacist.
- if you are allergic to acetaminophen or any of the inactive ingredients in this product.

Ask a doctor if you have liver disease

Ask a doctor or a pharmacist before use if you are taking the blood thinning drug warfarin

Stope use and ask a doctor if

- pain get worse or lasts more than 10 days
- fever gets worse or lasts more than 3 days
- new symptoms occur
- redness or swelling is present

These could be signs of a serious condition

PREGNANCY OR BREAST FEEDING

If pregnant or breast-feeding,ask a health professional before use.

Keep out of reach of children.

Overdose warning:In case of overdose, get medical help or contact a Poison Control Center right away. 1-800-222-1222 Quick medical attention is critical for adults as well as children even if you do not notice any signs or symptoms.

Directions

do not take more than directed (see overdose warning)

Age | Dose
adults and children 12 years and over | - take 1 tablespoonful (15 mL) every 6 hours as needed - do not take more than 4 tablespoonfuls in 24 hours, unless directed by a doctor - do not use for more than 10 days unless directed by a doctor
children under 12 years | ask a doctor

INACTIVE INGREDIENT

Inactive ingredientscitric acid, ethyl alcohol (0.16%), FD&C red #40, flavor, glycerin, methylparaben, propolyne glycol, propylparaben, sodium citrate, sodium saccharin, sucralose, sucrose, water

QUESTIONS

Questions?call 1-800-560-5223M-F 9 AM to 4 PM Eastern.